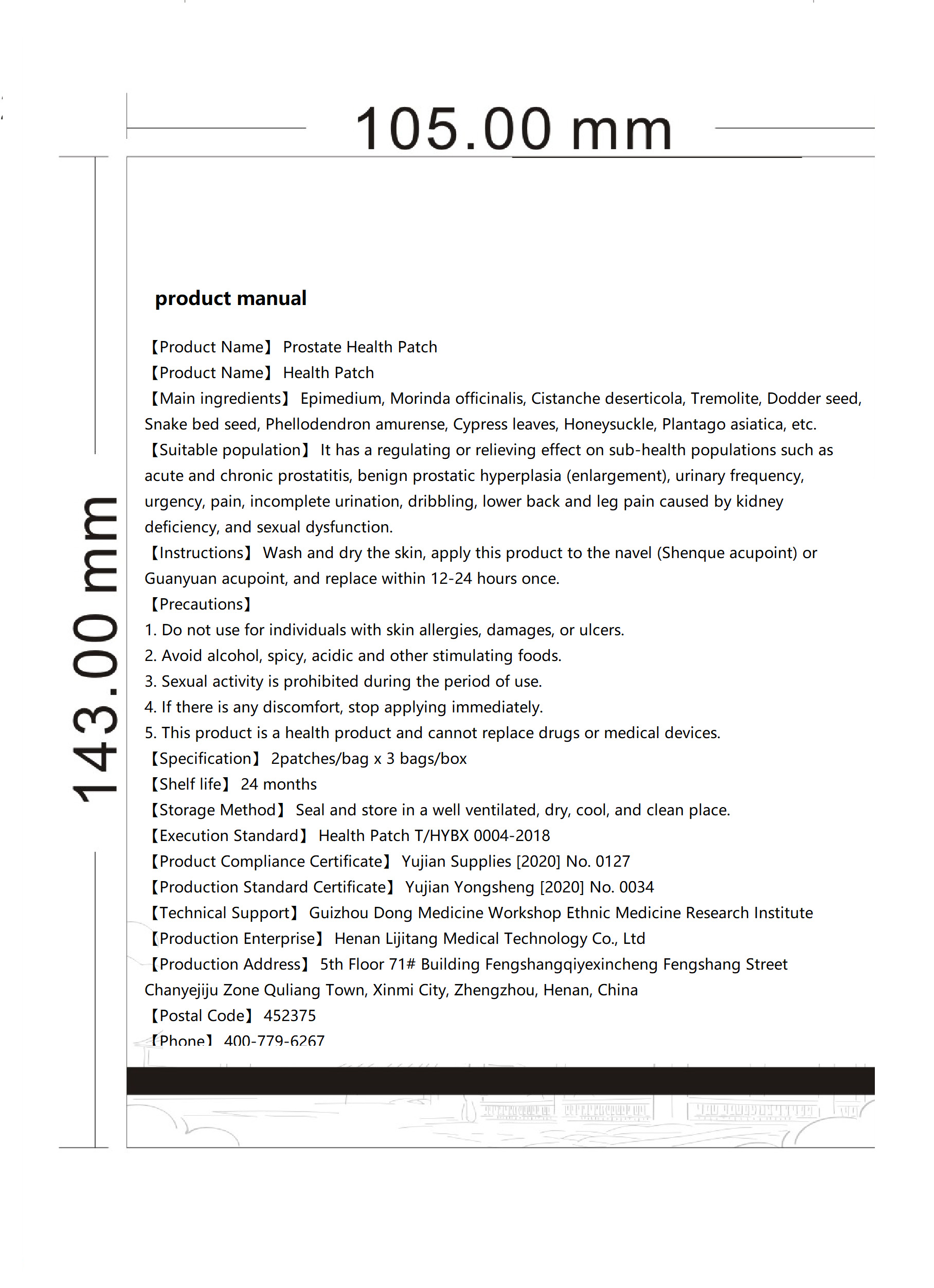 DRUG LABEL: Prostate Health Patch
NDC: 85305-003 | Form: PATCH
Manufacturer: Henan Lijitang Medical Technology Co., Ltd.
Category: homeopathic | Type: HUMAN OTC DRUG LABEL
Date: 20250724

ACTIVE INGREDIENTS: CISTANCHE DESERTICOLA WHOLE 0.035 g/1 1; CUSCUTA AUSTRALIS SEED 0.02 g/1 1; EPIMEDIUM PUBESCENS WHOLE 0.04 g/1 1; MORINDA OFFICINALIS WHOLE 0.04 g/1 1
INACTIVE INGREDIENTS: PHELLODENDRON AMURENSE BARK; CNIDIUM MONNIERI FRUIT OIL; PLANTAGO ASIATICA; LONICERA JAPONICA FLOWER; TREMOLITE; PLATYCLADUS ORIENTALIS LEAF

85305-003 Prostate Health Patch

ACTIVE INGREDIENT

Epimedium
Morinda officinalis
Cistanche deserticola
Actinolite
Dodder seed

PURPOSE

Prostate Health

INDICATIONS AND USAGE

Suitable for the crowd: for acute and chronicProstatitisprostatic hyperplasia (hypertrophy) andits caused byfrequent urination, urgency, urine pain,urine, urinedripping, due to kidney deficiency causedby lumbar acidleg pain, low sexual function, suchas sub-health groupswith conditioning or alleviation

Do not use for individuals with skin allergies, damages, or ulcers.

WHEN USING

Avoid alcohol, spicy, acidic and other stimulating foods.
Sexual activity is prohibited during the period of use.

lf there is any discomfort, stop applyingimmediately.

INACTIVE INGREDIENT

Snake bed seed
Phellodendron amurense
Cypress leaves
Honeysuckle
Plantago asiatica

DOSAGE AND ADMINISTRATION

【Instructions】 Wash and dry the skin, apply this product to the navel (Shenque acupoint) or Guanyuan acupoint, and replace within 12-24 hours once.